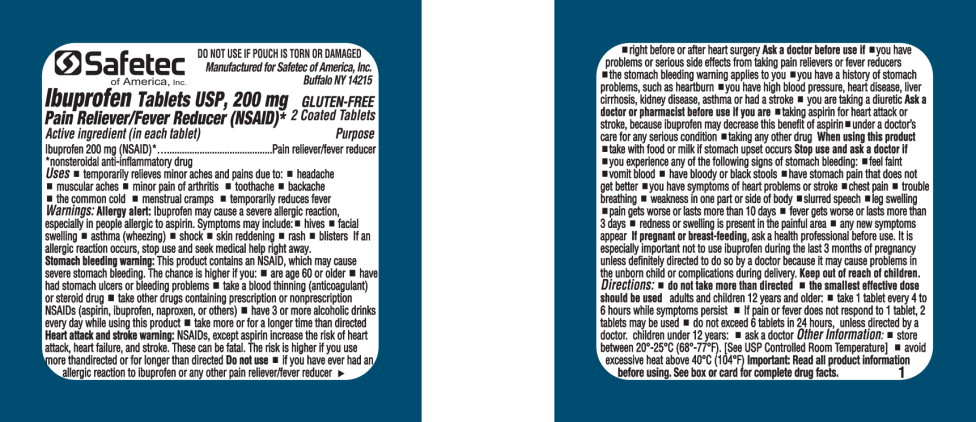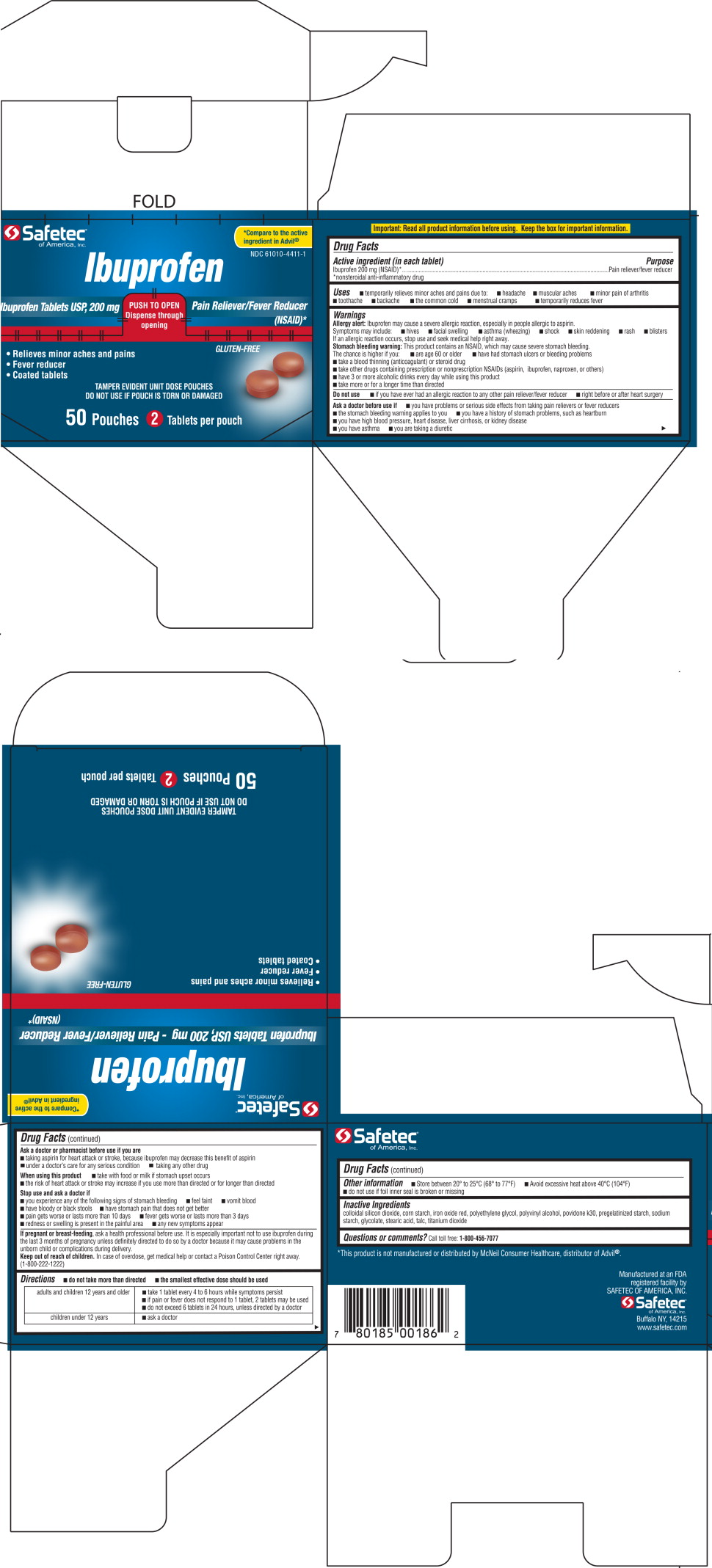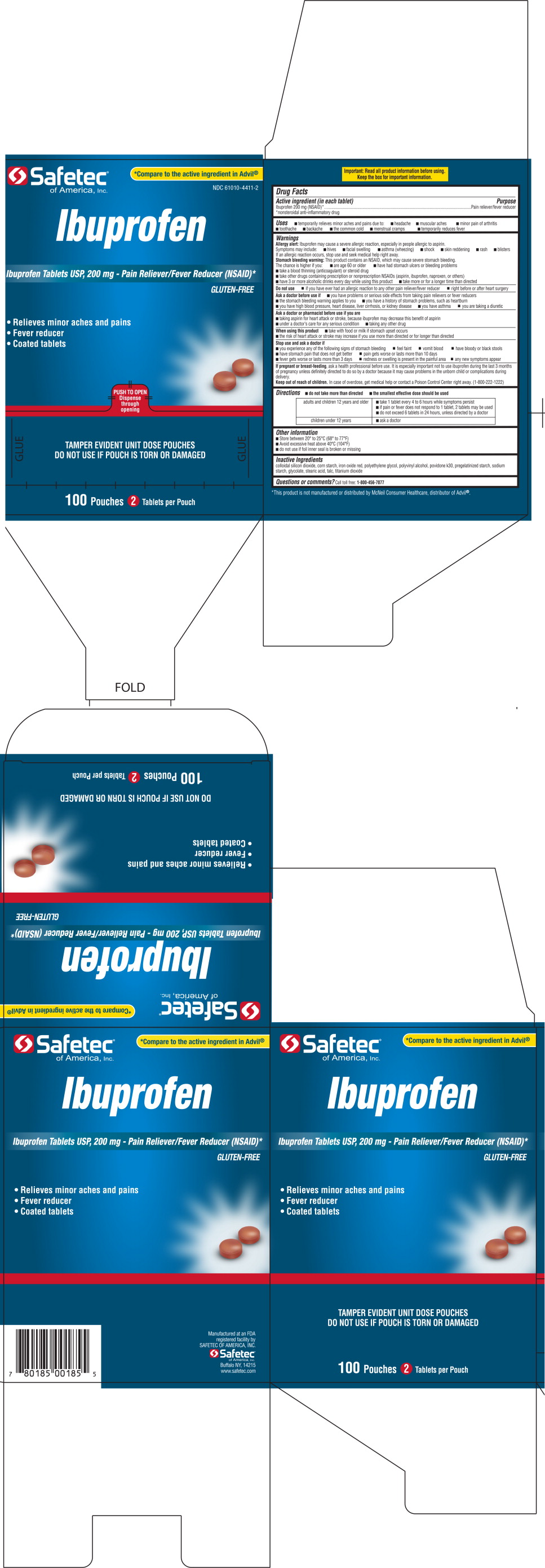 DRUG LABEL: Ibuprofen
NDC: 61010-4411 | Form: TABLET
Manufacturer: Safetec of America, Inc.
Category: otc | Type: HUMAN OTC DRUG LABEL
Date: 20191230

ACTIVE INGREDIENTS: Ibuprofen 200 mg/1 1
INACTIVE INGREDIENTS: Silicon Dioxide; Ferric Oxide Red; POLYETHYLENE GLYCOL 4000; Polyvinyl alcohol, Unspecified; Povidone K30; STARCH, CORN; Stearic acid; Sodium Starch Glycolate Type A Potato; Talc; Titanium dioxide

Drug Facts

Active ingredient (in each tablet)

Ibuprofen 200 mg (NSAID)*

*nonsteroidal anti-inflammatory drug

Purpose

Pain reliever/fever reducer

Uses

- temporarily relieves minor aches and pains due to:
- headache
- muscular aches
- minor pain of arthritis
- toothache
- backache
- the common cold
- menstrual cramps
- temporarily reduces fever

Warnings:

Allergy alert: Ibuprofen may cause a severe allergic reaction, especially in people allergic to aspirin. Symptoms may include:

- hives
- facial swelling
- asthma (wheezing)
- shock
- skin reddening
- rash
- blisters

If an allergic reaction occurs, stop use and seek medical help right away.

Stomach bleeding warning: This product contains an NSAID, which may cause severe stomach bleeding. The chance is higher if you:

- are age 60 or older
- have had stomach ulcers or bleeding problems
- take a blood thinning (anticoagulant) or steroid drug
- take other drugs containing prescription or nonprescription NSAIDs (aspirin, ibuprofen, naproxen, or others)
- have 3 or more alcoholic drinks every day while using this product
- take more or for a longer time than directed

Heart attack and stroke warning: NSAIDs, except aspirin increase the risk of heart attack, heart failure, and stroke. These can be fatal. The risk is higher if you use more than directed or for longer than directed

Do not use

- if you have ever had an allergic reaction to ibuprofen or any other pain reliever/fever reducer
- right before or after heart surgery

Ask a doctor before use if

- you have problems or serious side effects from taking pain relievers or fever reducers
- the stomach bleeding warning applies to you
- you have a history of stomach problems, such as heartburn
- you have high blood pressure, heart disease, liver cirrhosis, kidney disease, asthma or had a stroke
- you are taking a diuretic

Ask a doctor or pharmacist before use if you are

- taking aspirin for heart attack or stroke, because ibuprofen may decrease this benefit of aspirin
- under a doctor's care for any serious condition
- taking any other drug

When using this product

- take with food or milk if stomach upset occurs
- the risk of heart attack or stroke may increase if you use more than directed or for longer than directed

Stop use and ask a doctor if

- you experience any of the following signs of stomach bleeding:
- feel faint
- vomit blood
- have bloody or black stools
- have stomach pain that does not get better
- pain gets worse or lasts more than 10 days
- fever gets worse or lasts more than 3 days
- redness or swelling is present in the painful area
- any new symptoms appear

PREGNANCY OR BREAST FEEDING

If pregnant or breast-feeding, ask a health professional before use. It is especially important not to use ibuprofen during the last 3 months of pregnancy unless definitely directed to do so by a doctor because it may cause problems in the unborn child or complications during delivery.

Keep out of reach of children. In case of overdose, get medical help or contact a Poison Control Center right away. (1-800-222-1222)

Directions:

- do not lake more than directed
- the smallest effective dose should be used

adults and children 12 years and older | - take 1 tablet every 4 to 6 hours while symptoms persist - if pain or fever does not respond to 1 tablet, 2 tablets may be used - do not exceed 6 tablets in 24 hours, unless directed by a doctor,
children under 12 years | - ask a doctor

Other Information:

- Store between 20°-25°C (68°-77°F)
- Avoid excessive heat above 40°C (104°F)
- do not use if foil inner seal is broken or missing

Inactive Ingredients

colloidal silicon dioxide, corn starch, iron oxide red, polyethylene glycol, polyvinyl alcohol, povidone k30, pregelatinized starch, sodium starch, glycolate, stearic acid, talc, titanium dioxide

Questions or comments?

Call toll free: 1-800-456-7077

Principal Display Panel - 200 mg Pouch Label

Safetec
of America, Inc.

DO NOT USE IF POUCH IS TORN OR DAMAGED

Manufactured for Safetec of America, Inc.
Buffalo NY 14215

Ibuprofen Tablets USP, 200 mg
Pain Reliever/Fever Reducer (NSAID)*

GLUTEN-FREE
2 Coated Tablets

Principal Display Panel – 50 Pouches Carton Label

Safetec®
of America, Inc.

*Compare to the active ingredient in Advil®

NDC 61010-4411-1

Ibuprofen

Ibuprofen Tablets USP, 200 mg

PUSH TO OPEN

Dispense through opening

Pain Reliever/Fever Reducer (NSAID)*

- Relieves minor aches and pains
- Fever reducer
- Coated tablets

GLUTEN-FREE

TAMPER EVIDENT UNIT DOSE POUCHES

DO NOT USE IF POUCH IS TORN OR DAMAGED

50 Pouches 2 Tablets per pouch

Principal Display Panel – 100 Pouches Carton Label

Safetec®
of America, Inc.

*Compare to the active ingredient in Advil®

NDC 61010-4411-2

Ibuprofen

Ibuprofen Tablets USP, 200 mg - Pain Reliever/Fever Reducer (NSAID)*

GLUTEN-FREE

- Relieves minor aches and pains
- Fever reducer
- Coated tablets

PUSH TO OPEN

Dispense through opening

TAMPER EVIDENT UNIT DOSE POUCHES

DO NOT USE IF POUCH IS TORN OR DAMAGED

100 Pouches 2 Tablets per pouch